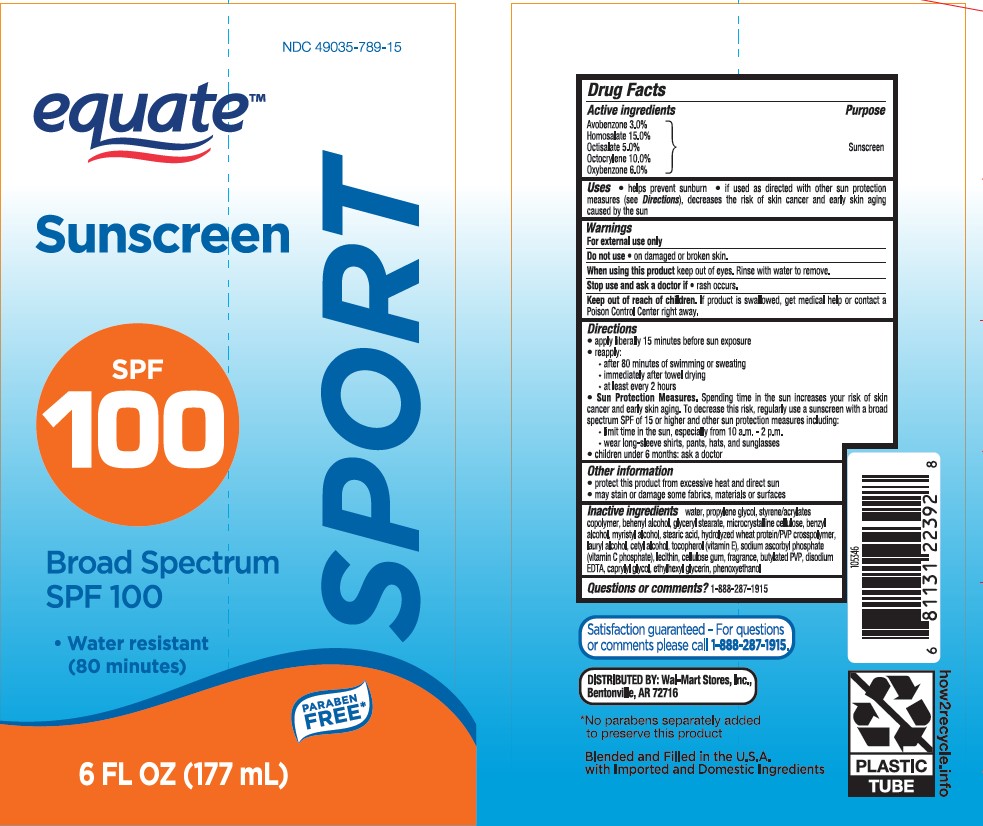 DRUG LABEL: Equate Sunscreen SPORT SPF 100
NDC: 49035-789 | Form: LOTION
Manufacturer: Walmart Stores Inc.
Category: otc | Type: HUMAN OTC DRUG LABEL
Date: 20241016

ACTIVE INGREDIENTS: AVOBENZONE 30 mg/1 mL; HOMOSALATE 150 mg/1 mL; OCTISALATE 50 mg/1 mL; OCTOCRYLENE 100 mg/1 mL; OXYBENZONE 60 mg/1 mL
INACTIVE INGREDIENTS: PROPYLENE GLYCOL; STYRENE/ACRYLAMIDE COPOLYMER (500000 MW); GLYCERYL STEARATE SE; MICROCRYSTALLINE CELLULOSE; BENZYL ALCOHOL; MYRISTYL ALCOHOL; STEARIC ACID; HYDROLYZED WHEAT PROTEIN (ENZYMATIC, 3000 MW); LAURYL ALCOHOL; CETYL ALCOHOL; .ALPHA.-TOCOPHEROL, DL-; SODIUM ASCORBYL PHOSPHATE; LECITHIN, SOYBEAN; CAPRYLYL GLYCOL; EDETATE DISODIUM; ETHYLHEXYLGLYCERIN; PHENOXYETHANOL; DOCOSANOL; CARBOXYMETHYLCELLULOSE SODIUM; WATER

Equate Sunscreen Sport SPF 100 Lotion

Active ingredients

Avobenzone 3.0%

Homosalate 15.0%

Octisalate 5.0%

Octocrylene 10.0%

Oxybenzone 6.0%

Purpose

Sunscreen

Uses

• helps prevent sunburn

• if used as directed with other sun protection measures (see Directions), decreases the risk of skin cancer and early skin aging caused by the sun

Warnings

For external use only

When using this product

keep out of eyes. Rinse with water to remove

Do not use

• on damaged or broken skin.

Stop use and ask a doctor if

• rash occurs.

Keep out of reach of children

If product is swallowed, get medical help or contact a Poison Control Center right away.

Directions

• apply liberally 15 minutes before sun exposure

• reapply:

• after 80 minutes of swimming or sweating

• immediately after towel drying

• at least every 2 hours

Sun Protection Measures. Spending time in the sun increases your risk of skin cancer and early skin aging. To decrease this risk, regularly use a sunscreen with a Broad Spectrum SPF value of 15 or higher and other sun protection measures including:

• limit time in the sun, especially from 10 a.m. - 2 p.m.

• wear long-sleeved shirts, pants, hats, and sunglasses

• children under 6 months: Ask a doctor

Other information

• protect the product in this container from excessive heat and direct sun

• may stain or damage some fabrics, materials or surfaces

Inactive ingredients

water, propylene glycol, styrene/acrylates copolymer, behenyl alcohol, glyceryl stearate, microcrystalline cellulose, benzyl alcohol, myristyl alcohol, stearic acid, hydrolyzed wheat protein/PVP crosspolymer, lauryl alcohol, cetyl alcohol, tocopherol (vitamin E), sodium ascorbyl phosphate (vitamin C phosphate), lecithin, cellulose gum, fragrance, butylated PVP, disodium EDTA, caprylyl glycol, ethylhexyl glycerin, phenoxyethanol